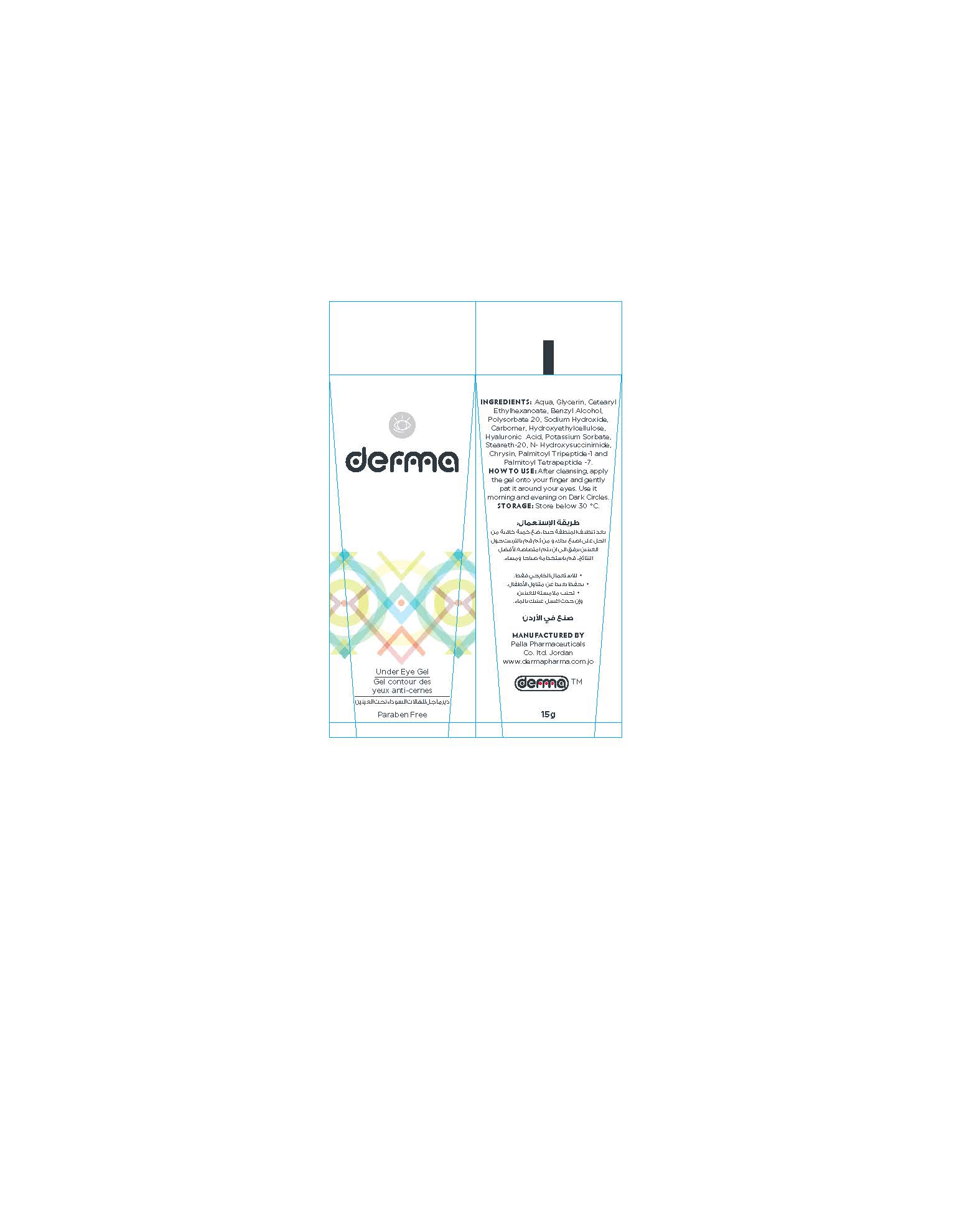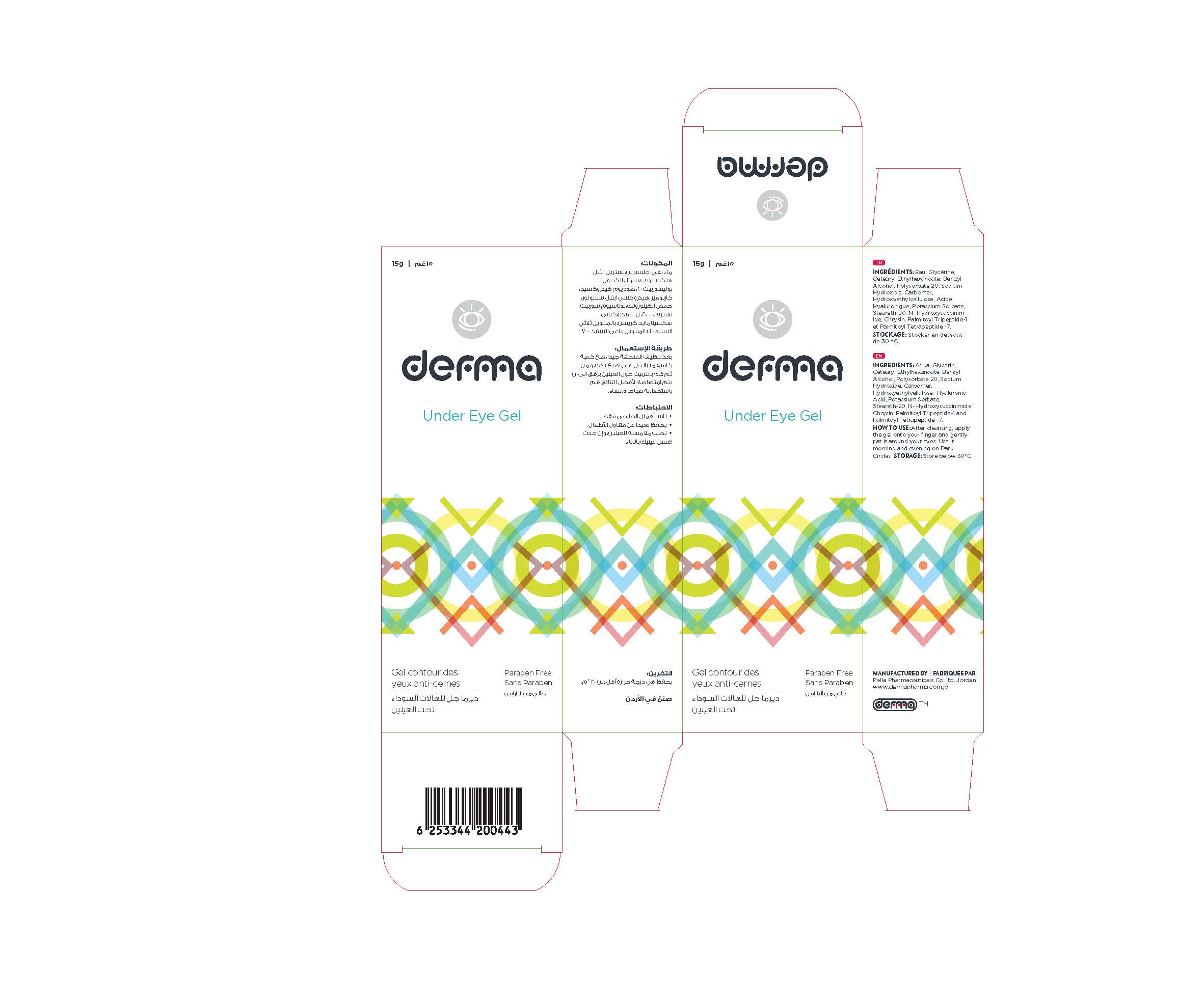 DRUG LABEL: Derma Under Eye
NDC: 82160-443 | Form: GEL
Manufacturer: Pella Pharmaceuticals Co. Ltd
Category: otc | Type: HUMAN OTC DRUG LABEL
Date: 20211129

ACTIVE INGREDIENTS: PALMITOYL TRIPEPTIDE-1 0.0003 mg/15 g; HYALURONIC ACID 0.15 mg/15 g; PALMITOYL TETRAPEPTIDE-7 0.00015 mg/15 g
INACTIVE INGREDIENTS: GLYCERIN; STEARETH-20; N-HYDROXYSUCCINIMIDE; CHRYSIN; POTASSIUM SORBATE; POLYSORBATE 20; CARBOMER 940; BENZYL ALCOHOL; HYDROXYETHYL CELLULOSE, UNSPECIFIED; WATER; CETEARYL ETHYLHEXANOATE; SODIUM HYDROXIDE

Under Eye

Forms and Presentation

Gel: Tube of 15 g.

Active Ingredients

Hyaluronic Acid

Palmitoyl Tripeptide-1

Palmitoyl Tetrapeptide-7

Inactive Ingredients

Aqua, Glycerin, Cetearyl Ethylhexanoate, Benzyl Alcohol, Polysorbate 20, Sodium Hydroxide, Carbomer, Hydroxyethylcellulose, Potassium Sorbate, Steareth-20, N- Hydroxysuccinimide, Chrysin.

Purpose

Under eye gel for dark circles

Properties

Under eye gel reduces dark circles and fine lines around the eye, therefore moisturizes and brightens it.
Paraben free.

Indications

Gel for Dark circles under eye.

Precautions

Keep out of reach of children

Warnings

- For external use only
- Avoid contact with eyes and mucous membranes.

Contraindications

Hypersensitivity to any of the components.

Side effects

There are no known side effects.

Dosage and administration

After cleansing, apply the gel onto your finger and gently pat it around your eyes. Use it morning and evening on Dark Circles.

Storage conditions

Store at a temperature below 30 °C.